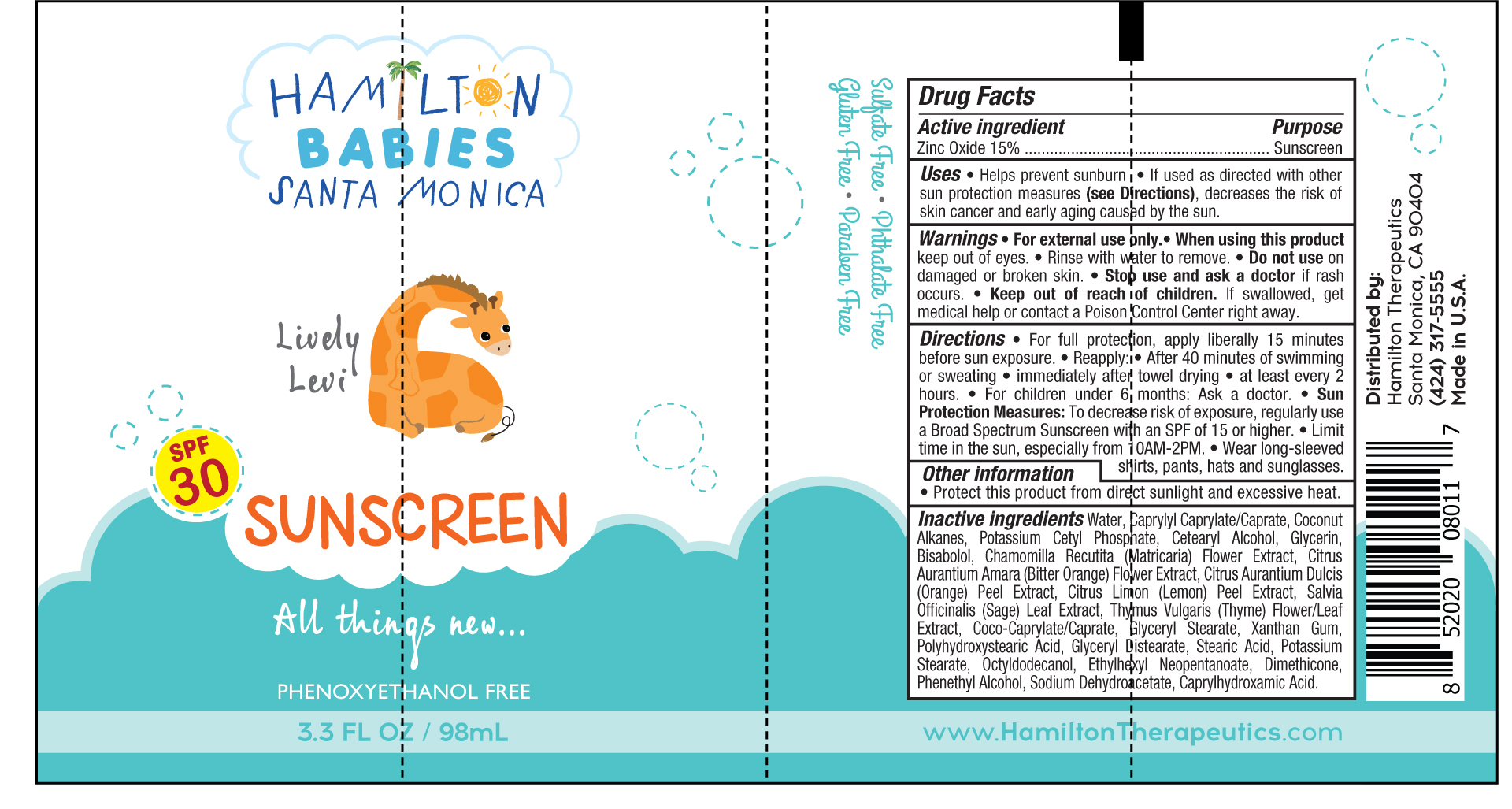 DRUG LABEL: Sunscreen SPF 30
NDC: 72381-102 | Form: CREAM
Manufacturer: Hamilton Therapeutics
Category: otc | Type: HUMAN OTC DRUG LABEL
Date: 20221130

ACTIVE INGREDIENTS: ZINC OXIDE 15 g/100 mL
INACTIVE INGREDIENTS: CITRUS AURANTIUM FLOWER; ORANGE PEEL; LEMON PEEL; SAGE; COCO-CAPRYLATE/CAPRATE; XANTHAN GUM; POLYHYDROXYSTEARIC ACID (2300 MW); POTASSIUM STEARATE; OCTYLDODECANOL; DIMETHICONE; PHENYLETHYL ALCOHOL; SODIUM DEHYDROACETATE; CAPRYLHYDROXAMIC ACID; CAPRYLYL CAPRYLATE/CAPRATE; COCONUT ALKANES; GLYCERYL DISTEARATE; WATER; CETOSTEARYL ALCOHOL; LEVOMENOL; GLYCERIN; CHAMOMILE; THYME; GLYCERYL MONOSTEARATE; POTASSIUM CETYL PHOSPHATE; STEARIC ACID

Sunscreen SPF 30

Active ingredient Purpose
Zinc Oxide 15% .......................................................... Sunscreen

Uses

• Helps prevent sunburn

• If used as directed with other sun protection measures (see Directions), decreases the risk of
skin cancer and early aging caused by the sun.

Keep out of reach of children. If swallowed, get medical help or contact a Poison Control Center right away.

• Stop use and ask a doctor if rash occurs.

Warnings

• For external use only

• When using this product keep out of eyes.

• Rinse with water to remove.

• Do not use on damaged or broken skin.

Directions

• For full protection, apply liberally 15 minutes before sun exposure.

• Reapply: • After 40 minutes of swimming or sweating • immediately after towel drying

• at least every 2 hours.

• For children under 6 months: Ask a doctor. • Sun Protection Measures: To decrease risk of exposure, regularly use a Broad Spectrum Sunscreen with an SPF of 15 or higher.

• Limit time in the sun, especially from 10AM-2PM.

• Wear long-sleeved shirts, pants, hats and sunglasses.

INACTIVE INGREDIENT

Inactive ingredients Water, Caprylyl Caprylate/Caprate, Coconut Alkanes, Potassium Cetyl Phosphate, Cetearyl Alcohol, Glycerin, Bisabolol, Chamomilla Recutita (Matricaria) Flower Extract, Citrus Aurantium Amara (Bitter Orange) Flower Extract, Citrus Aurantium Dulcis (Orange) Peel Extract, Citrus Limon (Lemon) Peel Extract, Salvia Officinalis (Sage) Leaf Extract, Thymus Vulgaris (Thyme) Flower/Leaf Extract, Coco-Caprylate/Caprate, Glyceryl Stearate, Xanthan Gum, Polyhydroxystearic Acid, Glyceryl Distearate, Stearic Acid, Potassium Stearate, Octyldodecanol, Ethylhexyl Neopentanoate, Dimethicone, Phenethyl Alcohol, Sodium Dehydroacetate, Caprylhydroxamic Acid.

PACKAGE LABEL

SPF 30 Sunscreen

3.3FL OZ / 98mL